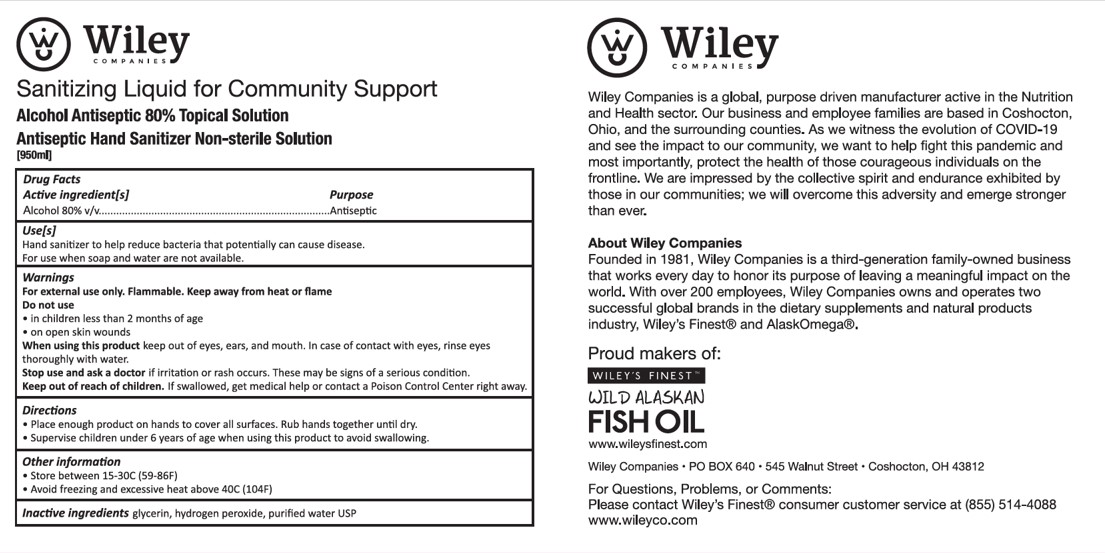 DRUG LABEL: Sanitizing Liquid for Community Support
NDC: 74145-001 | Form: LIQUID
Manufacturer: Wiley Organics, Inc.
Category: otc | Type: HUMAN OTC DRUG LABEL
Date: 20200323

ACTIVE INGREDIENTS: ALCOHOL 80 mL/100 mL
INACTIVE INGREDIENTS: GLYCERIN; HYDROGEN PEROXIDE; WATER

Alcohol Antiseptic 80% Topical Solution

Active Ingredient

Ethanol 80%

Purpose

Antiseptic, Hand Sanitizer

Use

Hand Sanitizer to help reduce bacteria that can potentially cause disease. For use when soap and water are not available.

Warning

For external use only. Flammable. Keep away from heat or flame

Do not use

- in children less than 2 months of age.
- on open skin wounds.

Stop use Section

Stop use and ask a doctor if irritation or rash occurs. These may be signs of a serious condition.

KEEP OUT OF REACH OF CHILDREN

Keep out of each of children. If swallowed, get medical help or contact a poison control center right away.

Directions

Place enough product on hands to cover all surfaces. Rub hands together until dry.

Surpervise children under 6 years of age when using this product to avoid swallowing.

Oter Information

Store between 15-30 C (59-86F)

Avoid freezing and excessive heat above 40C (104F)

Inactive Ingredients

glycerin, hydrogen peroxide, purified water USP

PACKAGE LABEL

NDC 74145-001-01